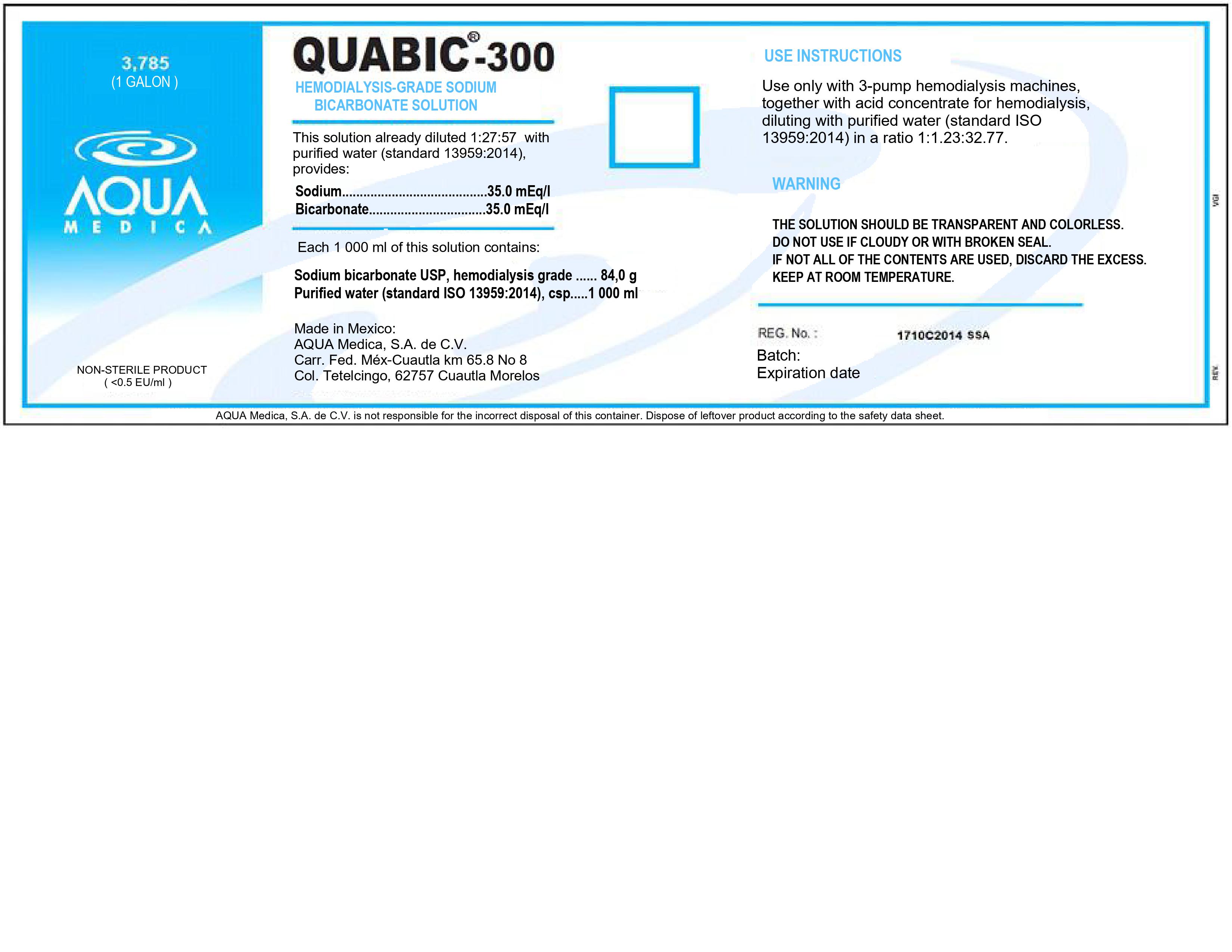 DRUG LABEL: QUABIC-300
NDC: 81943-502 | Form: SOLUTION, CONCENTRATE
Manufacturer: Aqua Medica, S.A. de C.V.
Category: otc | Type: HUMAN OTC DRUG LABEL
Date: 20251110

ACTIVE INGREDIENTS: SODIUM BICARBONATE 8.4 g/100 mL
INACTIVE INGREDIENTS: WATER

This is a Hemodialysis-Grade Sodium Bicarbonate Solution.

This solution already diluted 1:27:57 with purified water (standard 13959:2014), provides:

Sodium: 35.0 mEq/l

Bicarbonate: 35.0 mEq/l

Each 1000 mL of this solution contains:

Sodium bicarbonate USP, hemodialysis grade: 84.0 g

Purified water (standard ISO 13959:2014), csp: 1000 mL

Active Ingredient(s)

Sodium Bicarbonate: Antiseptic

Purpose

For use only with 3-pump hemodialysis machines.

Use

Use oly with 3-pump hemodialysis machines, together with acid concentrate for hemodialysis, diluting with purified water (standard ISO 13959:2014) IN A RATIO 1:1.23:32.77.

Warnings

The solution should be transparent and colorless. Do not use if cloudy or with broken seal. If not all of the contents are used, discard the excess. Keep at room temperature.

DOSAGE AND ADMINISTRATION

For use only with 3-pump hemodialysis machines, together with acid concentrate for hemodialysis, diluting with purified water.

Do not use

- If cloudy or with broken seal.

WHEN USING

If not all of the contents are used, discard the excess.

Keep out of reach of children. If swallowed, get medical help or contact a Poison Control Center right away.

Other information

- Keep at room temperature.

Inactive ingredients

Purified water (standard ISO 13959:2014)

RECENT MAJOR CHANGES

Use only with 3-pump hemodialysis machines.

Package Label - Principal Display Panel

3785 mL NDC: 81943-502-01